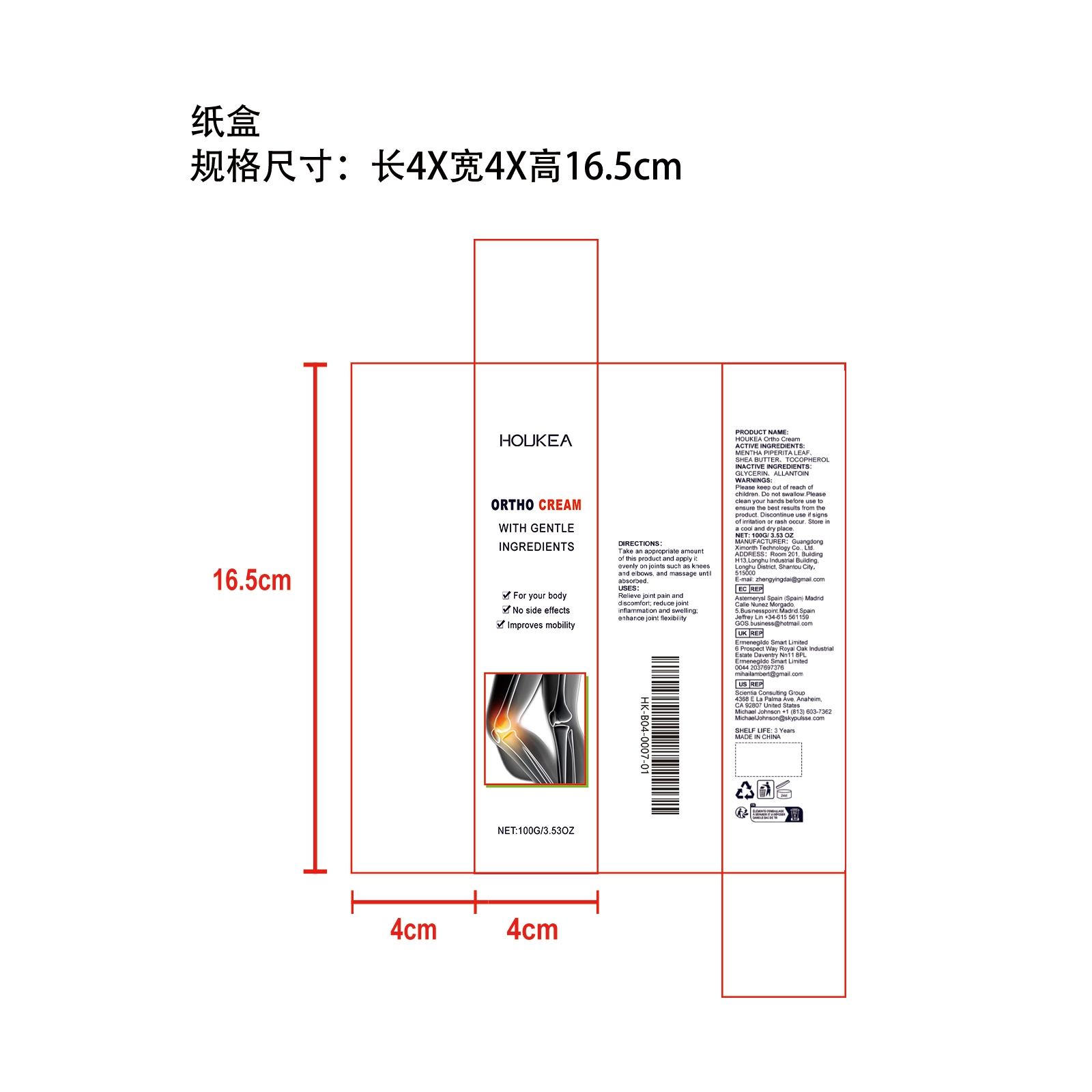 DRUG LABEL: HOUKEA Ortho Cream
NDC: 84660-080 | Form: CREAM
Manufacturer: Guangdong Ximonth Technology Co., Ltd.
Category: otc | Type: HUMAN OTC DRUG LABEL
Date: 20241021

ACTIVE INGREDIENTS: TOCOPHEROL 10 g/100 g; SHEA BUTTER 15 g/100 g; MENTHA PIPERITA LEAF 20 g/100 g
INACTIVE INGREDIENTS: ALLANTOIN 25 g/100 g; GLYCERIN 30 g/100 g

Active Ingredient(s)

MENTHA PIPERITA LEAF、SHEA BUTTER、TOCOPHEROL

Purpose

Improves mobility

Use

Take an appropriate amount of this product and apply it evenly on joints such as knees and elbows, and massage until absorbed.

Warnings

Please keep out of reach of children.Do not swallow.Please clean your hands before use to ensure the best results from the product.Discontinue use if signs of irritation or rash occur.Store in a cool and dry place.

Do not use

Discontinue use if signs of irritation or rash occur.

STOP USE

Discontinue use if signs of irritation or rash occur

KEEP OUT OF REACH OF CHILDREN

Please keep out of reach of children. Do not swallow.

STORAGE AND HANDLING

Avoid freezing and excessive heat above 40C (104F) ）
Store in a cool and dry place.

INACTIVE INGREDIENT

GLYCERIN、ALLANTOIN